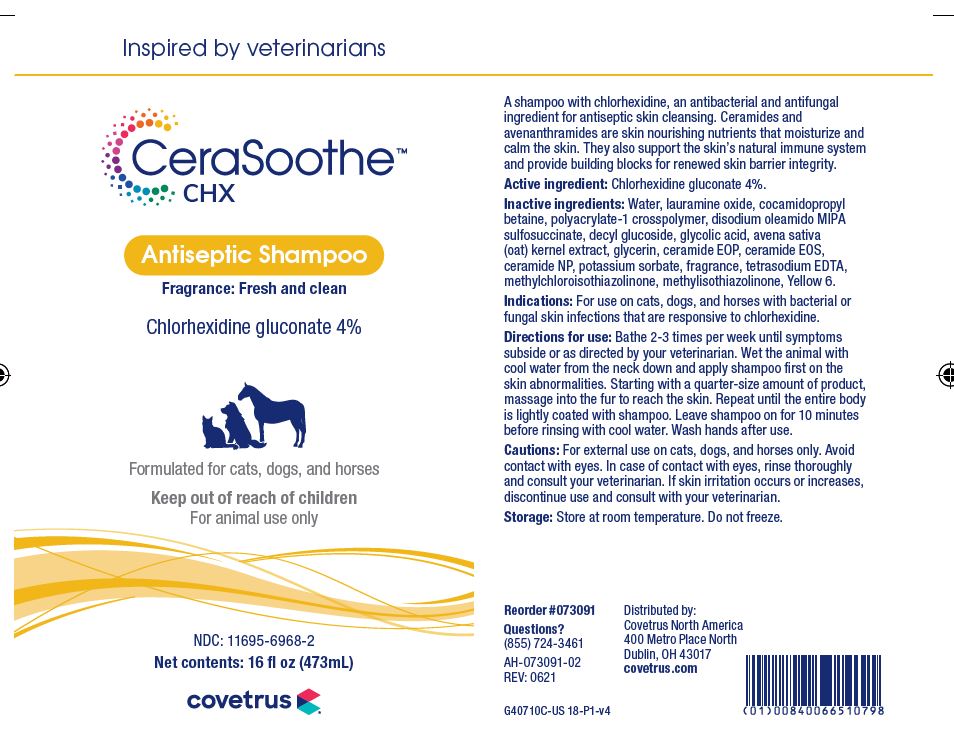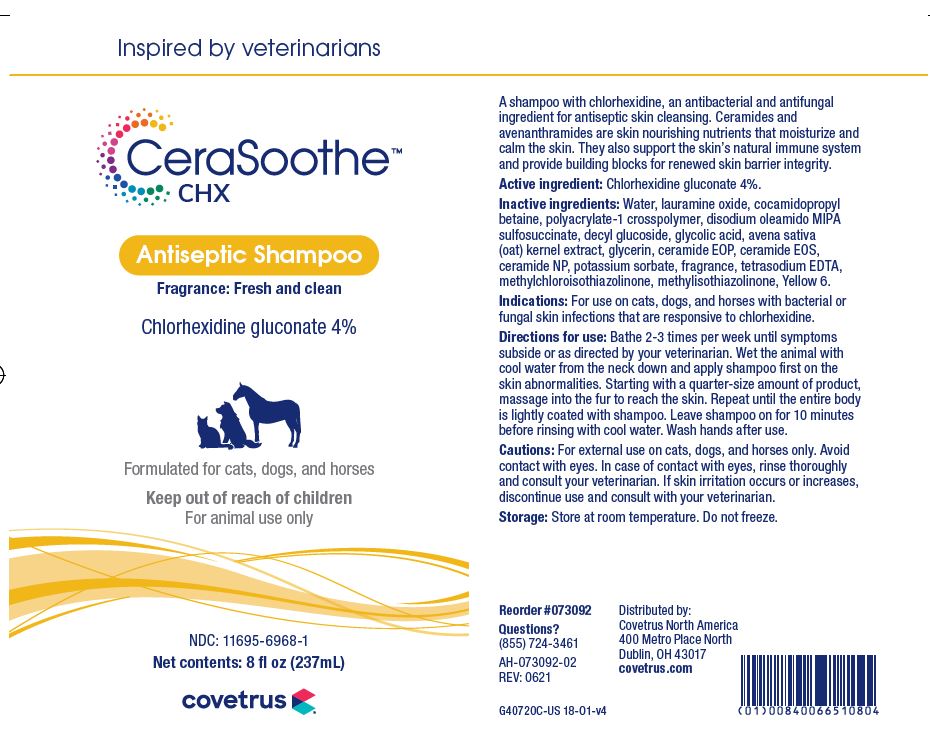 DRUG LABEL: CeraSoothe
NDC: 11695-6968 | Form: SHAMPOO
Manufacturer: BUTLER ANIMAL HEALTH SUPPLY, LLC DBA COVETRUS NORTH AMERICA
Category: animal | Type: OTC ANIMAL DRUG LABEL
Date: 20220523

ACTIVE INGREDIENTS: CHLORHEXIDINE GLUCONATE 40 mg/1 mL
INACTIVE INGREDIENTS: WATER; LAURAMINE OXIDE; COCAMIDOPROPYL BETAINE; CARBOMER HOMOPOLYMER, UNSPECIFIED TYPE; DISODIUM OLEAMIDO MIPA-SULFOSUCCINATE; DECYL GLUCOSIDE; GLYCOLIC ACID; AVENANTHRAMIDES; GLYCERIN; CERAMIDE 1; CERAMIDE EOS; CERAMIDE NP; POTASSIUM SORBATE; EDETATE SODIUM; METHYLCHLOROISOTHIAZOLINONE; METHYLISOTHIAZOLINONE

DESCRIPTION

CeraSoothe CHX

Antiseptic Shampoo

Fragrance: Fresh and clean

Chlorhexidine gluconate 4%

Formulated for cats, dogs and horses

Keep out of reach of children

For animal use only

A shampoo with chlorhexidine, an antibacterial and antifungal ingredient for antiseptic skin cleansing. Ceramides and avenanthramides are skin nourishing nutrients that moisturize and calm the skin. They also support the skin's natural immune system and provide building blocks for renewed skin barrier integrity.

Active ingredient: Chlorhexidine gluconate 4%

Inactive ingredients: Water, lauramine oxide, cocamidopropyl betaine, polyacrylate-1 crosspolymer, disodium oleamido MIPA sulfosuccinate, decyl glucoside, glycolic acid, avena sativa (oat) kernal extract, glycerin, ceramide EOS, ceramide EOP, ceramide NP, potassium sorbate, fragrance, tetrasodium EDTA, sodium chloride, methylchloroisothiazolinone, methylisothiazolinone, Yellow 6.

INDICATIONS AND USAGE

Indications: For use on cats, dogs and horses with bacterial or fungal skin infections responsive to chlorhexidine.

Directions for use: Bathe 2-3 times per week until symptoms subside or as directed by your veterinarian. Wet the animal with cool water from the neck down and apply the shampoo first on the skin abnormalities. Starting with a quarter-size amount of product, massage in the fur to reach the skin. Repeat until the entire body is lightly coated with shampoo. Leave shampoo on for 10 minutes before rinsing with cool water. Wash hands after use.

WARNINGS AND PRECAUTIONS

Cautions: For external use on cats, dogs and horses only. Avoid contact with eyes. In case of contact with eyes, rinse thoroughly and consult your veterinarian. If skin irritation occurs or increases, discontinue use and consult your veterinarian.

STORAGE AND HANDLING

STORAGE CONDITIONS: Store at room temperature. Do not freeze.

Distributed by:

Covetrus North America

400 Metro Place North

Dublin, OH 43107

covetrus.com

Questions?

(855) 724-3461

PRINCIPAL DISPLAY PANEL - 8 OUNCE (237 mL) Bottle

Inspired by veterinarians

CeraSoothe CHX

Antiseptic Shampoo

Fragrance: Fresh and clean

Chlorhexidine gluconate 4%

Formulated for cats, dogs and horses

Keep out of reach of children

For animal use only

NDC 11695-6968-1

Net Contents: 8 FL. OZ. (237 mL)

covetrus

PRINCIPAL DISPLAY PANEL - 16 OUNCE (473 mL) Bottle

Inspired by veterinarians

CeraSoothe CHX

Antiseptic Shampoo

Fragrance: Fresh and clean

Chlorhexidine gluconate 4%

Formulated for cats, dogs and horses

Keep out of reach of children

For animal use only

NDC 11695-6968-2

Net Content: 16 FL. OZ. (473 mL)

covetrus